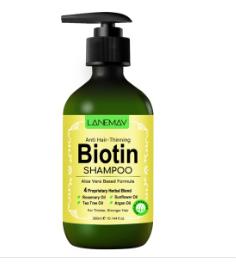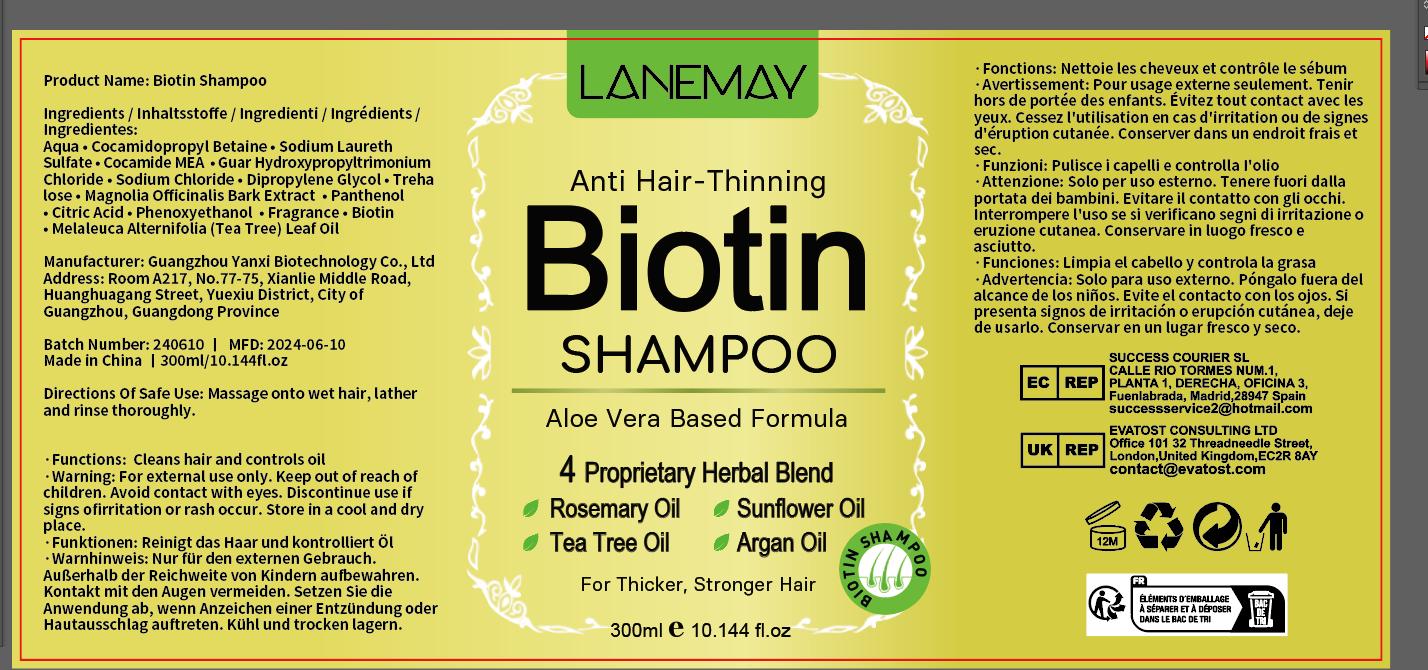 DRUG LABEL: BiotinShampoo
NDC: 84025-058 | Form: SHAMPOO
Manufacturer: Guangzhou Yanxi Biotechnology Co., Ltd
Category: otc | Type: HUMAN OTC DRUG LABEL
Date: 20240710

ACTIVE INGREDIENTS: BIOTIN 4 mg/300 mL; COCAMIDOPROPYL BETAINE 2 mg/300 mL
INACTIVE INGREDIENTS: WATER

DOSAGE AND ADMINISTRATION

use as a normal hair cream

WARNINGS

Keep out of Children

INACTIVE INGREDIENT

Aqua

INDICATIONS AND USAGE

For daily hair care

Keep out of Children

PURPOSE

strong and nourishing hair